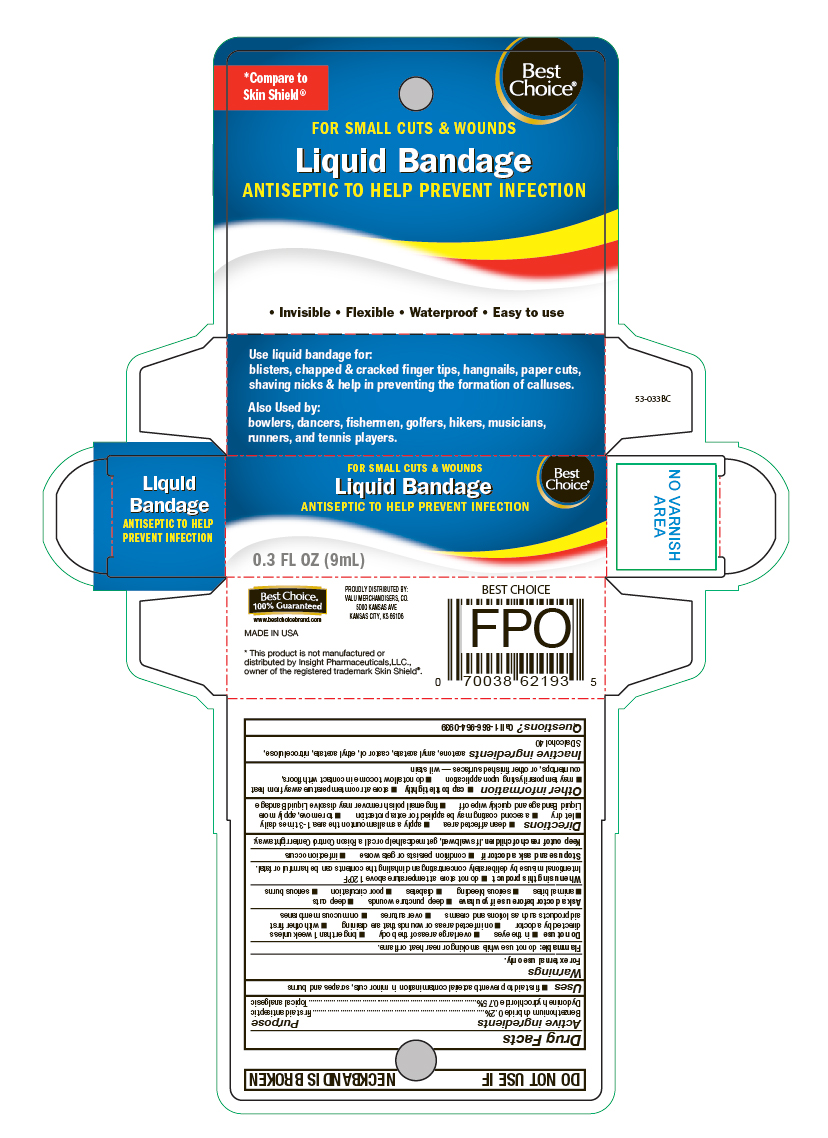 DRUG LABEL: Benzethonium chloride Plus Dyclonine hydrochloride
NDC: 63941-546 | Form: LIQUID
Manufacturer: VALU MERCHANDISERS, CO
Category: otc | Type: HUMAN OTC DRUG LABEL
Date: 20251124

ACTIVE INGREDIENTS: BENZETHONIUM CHLORIDE 0.2 mg/9 mL; DYCLONINE HYDROCHLORIDE 0.75 mg/9 mL
INACTIVE INGREDIENTS: ACETONE; AMYL ACETATE; CASTOR OIL; ETHYL ACETATE; PYROXYLIN; ALCOHOL

Best Choice Liquid Bandage

Active ingredients

Benzethonium chloride 0.2%

Dyclonine hydrochloride 0.75%

Purpose

First aid antiseptic

Topical analgesic

Uses

- first aid to prevent bacteria contamination in minor cuts and scrapes

Warnings

For external use only.

Flammable:

do not use while smoking or near heat or flame.

Do not use

- in the eyes
- over large areas of the body
- longer than 1 week unless directed by a doctor
- on infected areas or wounds that are draining
- with other first aid products such as lotions and creams
- over sutures
- on mucous membranes

Ask a doctor before use if you have

- deep puncture wounds
- deep cuts
- animal bites
- serious bleeding
- diabetes
- poor circulation
- serious burns

When using this product

- do not sotre at temperaure above 120oF

Intentional misuse by deliberately concentrating and inhaling the contents can be harmful or fatal.

Stop use and ask a doctor if

- conditions persists or gets worse
- infection occurs

Keep out of reach of children.

If swallowed, get medical help or call a Poison Control Center right away.

Directions

- Clean affected area
- apply a small amount on the area 1-3 times daily
- let dry
- a second coating may be applied for extra protection
- to remove, apply more Liquid Bandage and quickly wipe off
- finger nail polish remover may dissolve Liquid Bandage

Other information

- cap bottle tightly
- store at room temperature away from heat
- may temporarily sting upon application
- do not allow to come in contact with floors, countertops, or other finished surfaces - will stain

Inactive ingredients

acetone, amyl acetate, castor oil, ethyl acetate, nitrocellulose, SD slcohol 40

Questions

Call 1-866-964-0939

Principal Display Panel

Best Choice

For Small Cuts & Wounds

Liquid Bandage

Antiseptic to Help Prevent Infection

- Invisible
- Flexible
- Waterproof
- Easy to use

Use liquid bandage for:

blisters, chapped & cracked finger tips, hangnails, paper cuts, shaving nicks & help in preventing the formation of calluses.

Also Used by:

bowlers, dancers, fishermen, golfers, hikers, musicians, runners and tennis players.

0.3 FL OZ (9 mL)